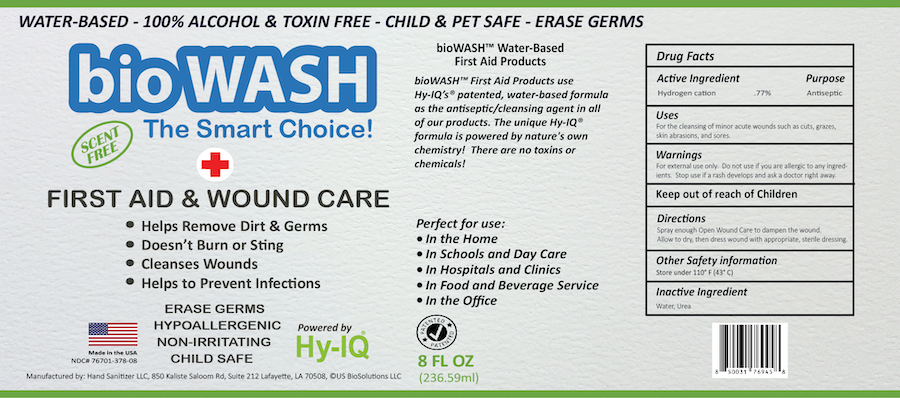 DRUG LABEL: BioWash First Aid and Wound Care
NDC: 76701-378 | Form: SPRAY
Manufacturer: Hand Sanitizer LLC
Category: otc | Type: HUMAN OTC DRUG LABEL
Date: 20210821

ACTIVE INGREDIENTS: HYDROGEN CATION 10 mg/1 mL
INACTIVE INGREDIENTS: WATER 940 mg/1 mL; UREA 50 mg/1 mL

BioWash First Aid and Wound Care

Active Ingredient

Hydrogen Cation .77%

Purpose

Antiseptic

Uses

For the cleansing of minor acute wounds such as cuts, grazes, akin abrasions, and sores.

Warnings

For external use only. Do not use if you are allergic to any ingredients. Stop use if rash develops and ask a doctor right away.

Keep Out of Reach of Children

Directions

Spray enough Open Wound Care to dampen the wound.Allow to dry, then dress wound with appropriate, sterile dressing.

Other Safety Information

Store under 110º F (43º C)

Inactive Ingredient

Water, Urea